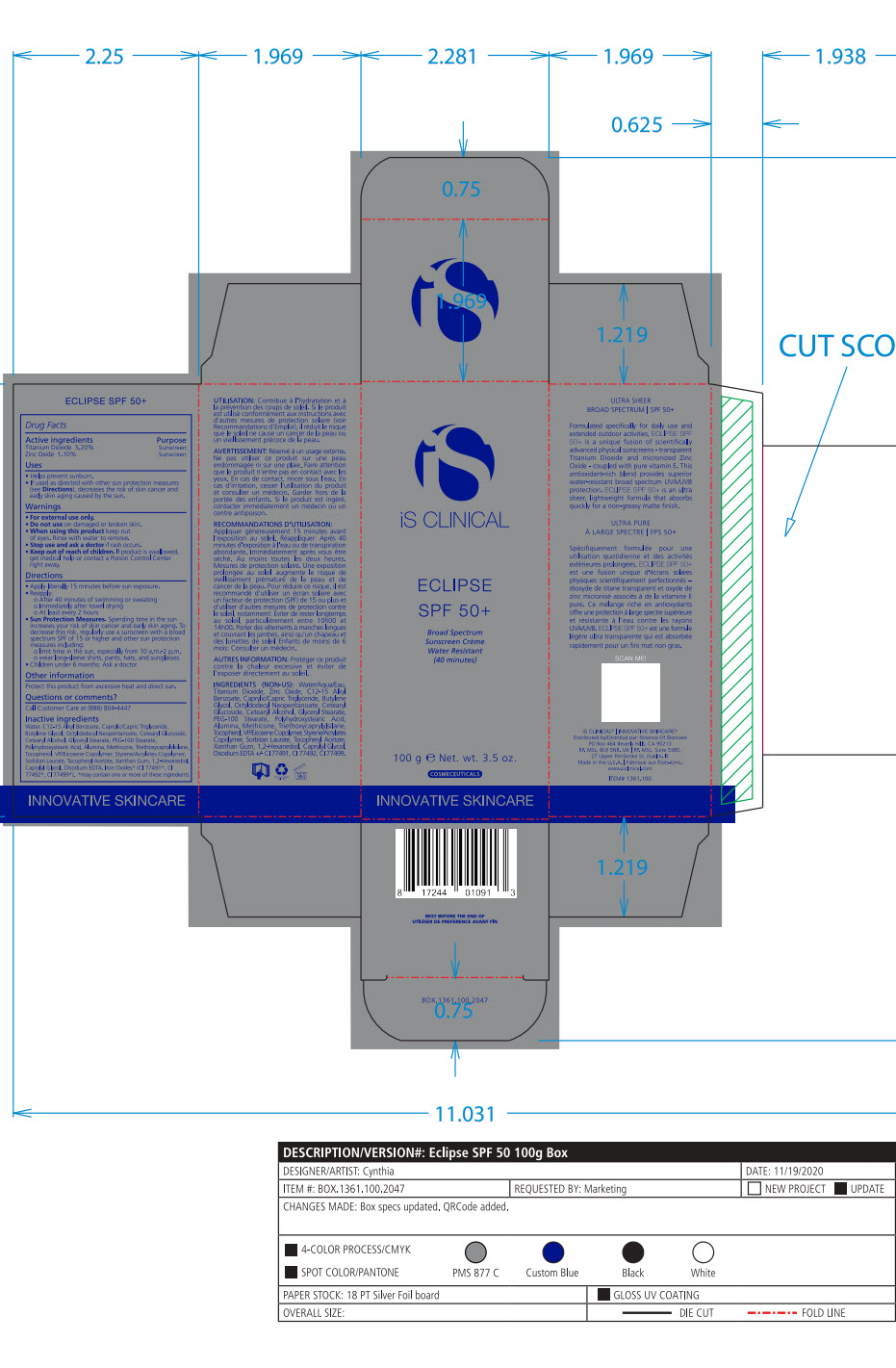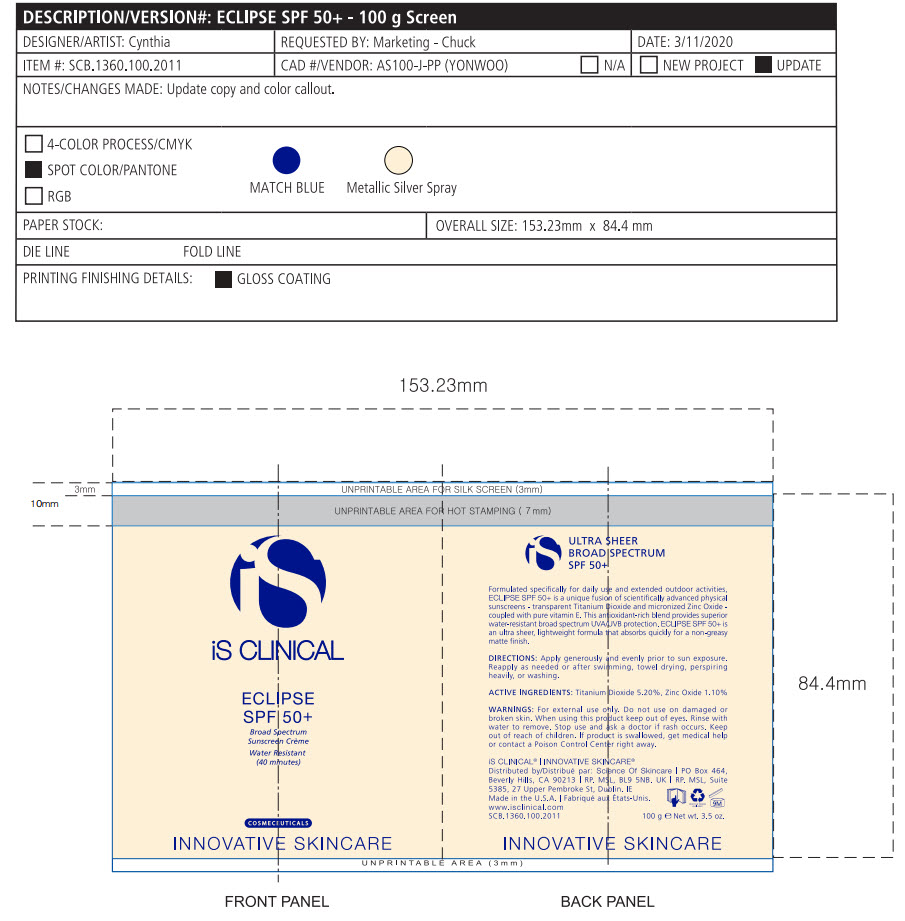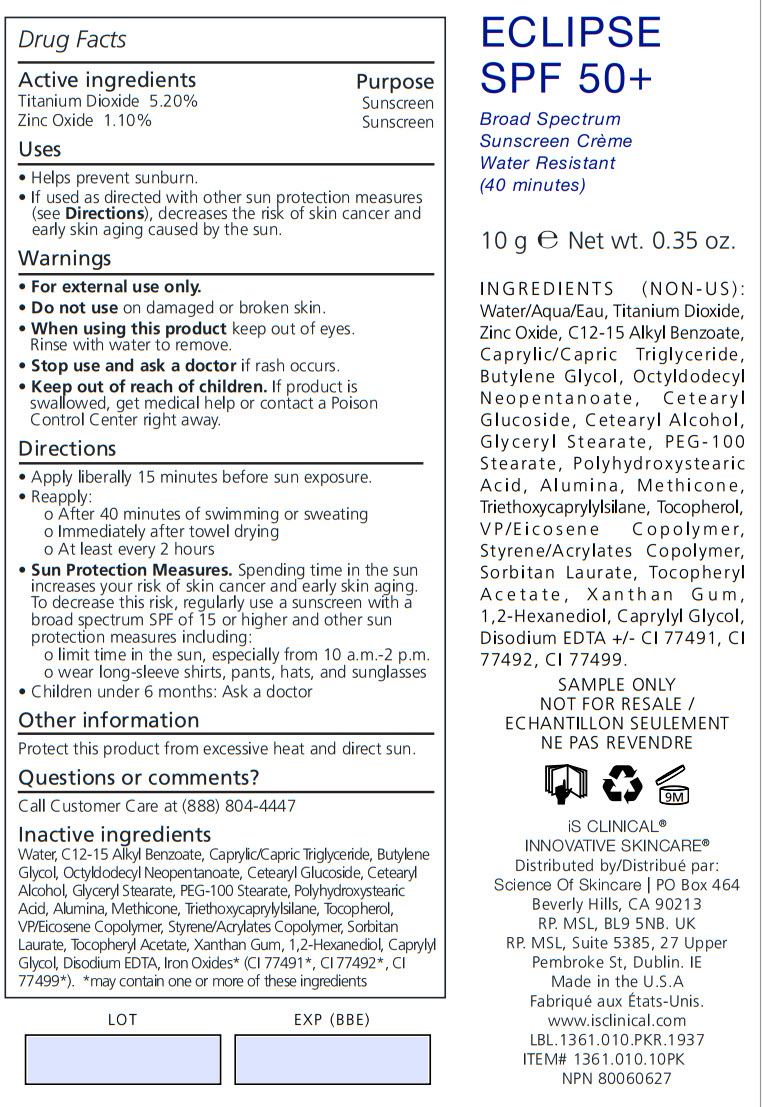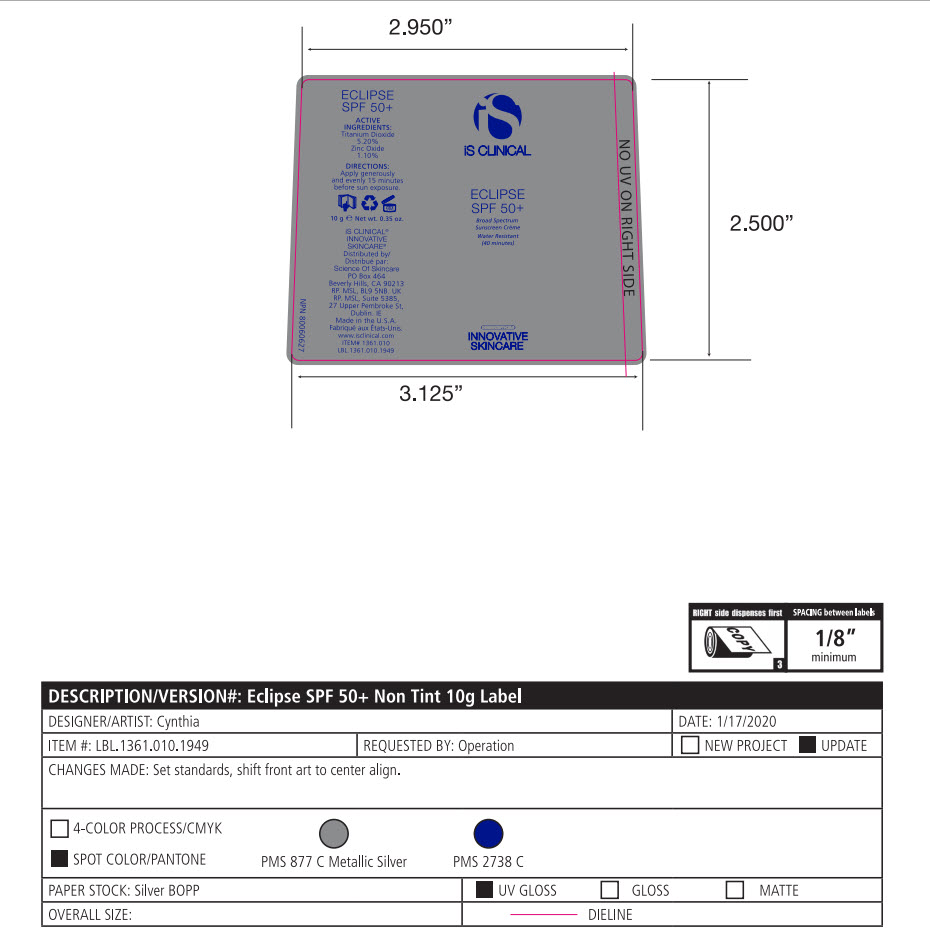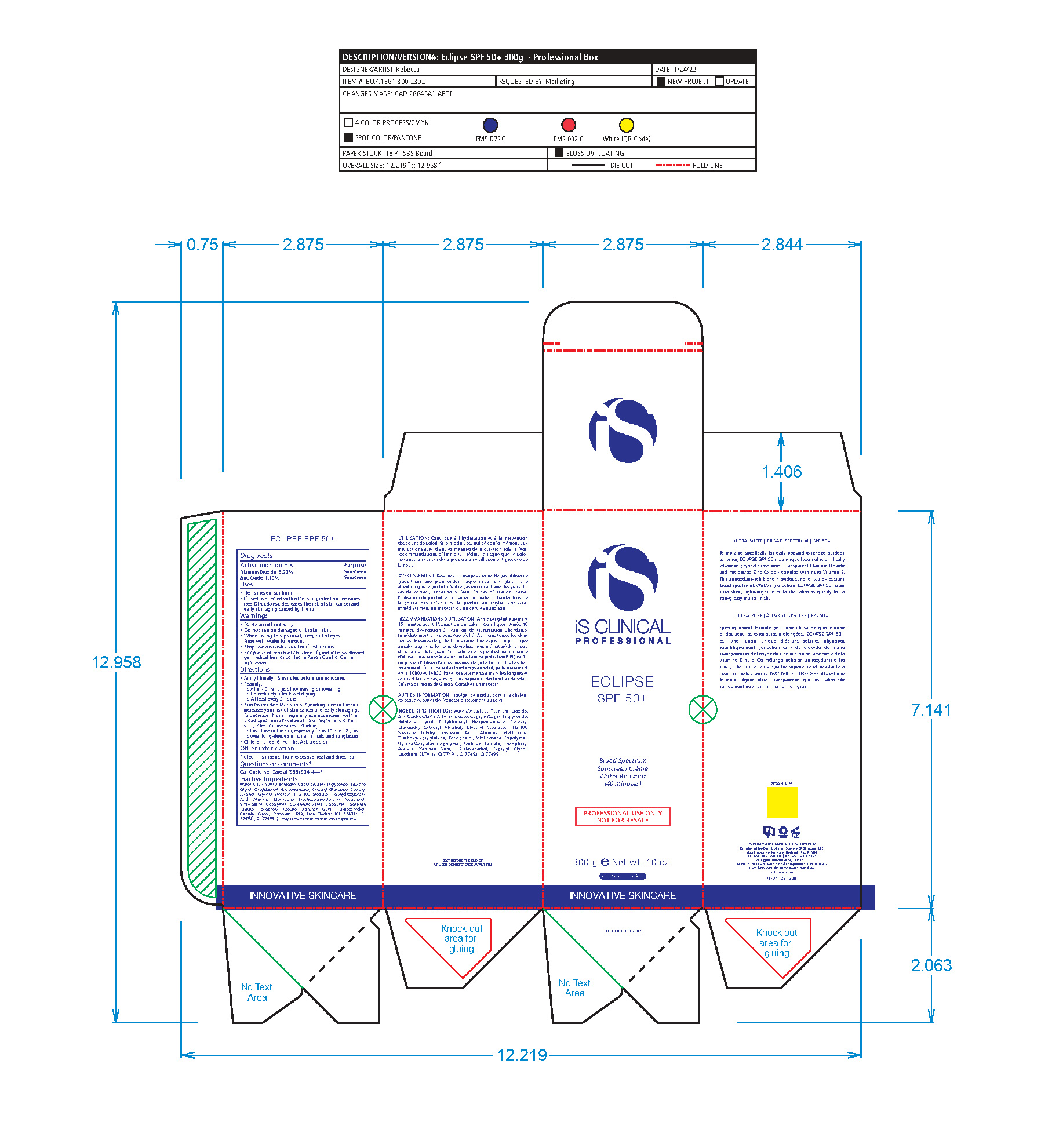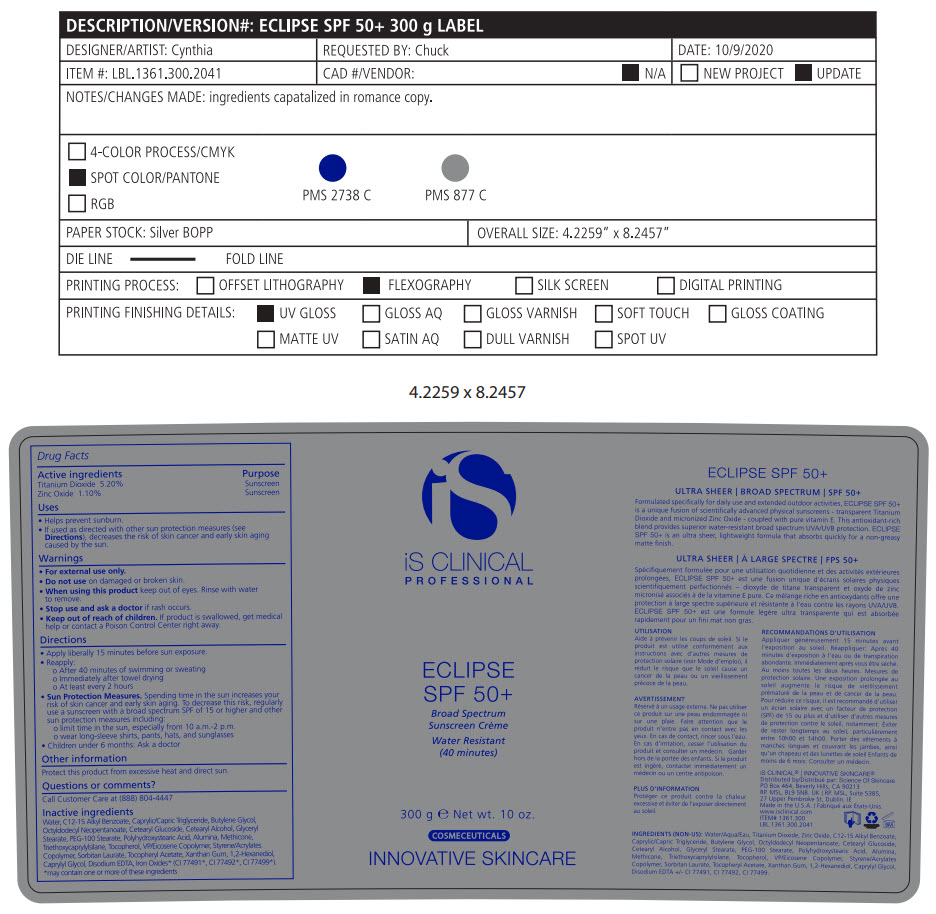 DRUG LABEL: ECLIPSE SPF 50
NDC: 69219-102 | Form: LOTION
Manufacturer: SCIENCE OF SKINCARE LLC
Category: otc | Type: HUMAN OTC DRUG LABEL
Date: 20250109

ACTIVE INGREDIENTS: TITANIUM DIOXIDE 5.2 g/100 g; ZINC OXIDE 1.1 g/100 g
INACTIVE INGREDIENTS: PEG-100 STEARATE; POLYHYDROXYSTEARIC ACID (2300 MW); SORBITAN MONOLAURATE; STYRENE; TOCOPHEROL; .ALPHA.-TOCOPHEROL ACETATE; TRIETHOXYCAPRYLYLSILANE; VINYLPYRROLIDONE/EICOSENE COPOLYMER; WATER; XANTHAN GUM; FERRIC OXIDE RED; FERROSOFERRIC OXIDE; FERRIC OXIDE YELLOW; 1,2-HEXANEDIOL; ALUMINUM; BUTYLENE GLYCOL; ALKYL (C12-15) BENZOATE; MEDIUM-CHAIN TRIGLYCERIDES; CAPRYLYL GLYCOL; CETOSTEARYL ALCOHOL; CETEARYL GLUCOSIDE; EDETATE DISODIUM; GLYCERYL MONOSTEARATE; OCTYLDODECYL NEOPENTANOATE

Eclipse SPF 50 Non Tinted

Active Ingredients

TITANIUM DIOXIDE – 5.20%

Zinc Oxide – 1.10%

PURPOSE

SUNSCREEN

USES

• Helps hydrate and prevent sunburn.
• If used as directed with other sun protection measures (see Directions), decreases the risk of skin cancer and early skin aging caused by the sun

WARNINGS

• For external use only

• Do not use on damaged or broken skin

• When using this product keep out of eyes. Rinse with water to remove

• Stop use and ask a doctor if rash occurs

- Keep out of reach of children. If product is swallowed,get medical help or contact a Poison Control Center right away.

DIRECTIONS

- APPLY LIBERALLY 15 MINUTES BEFORE SUN EXPOSURE.
- REAPPLY:
- AFTER 40 MINUTES OF SWIMMING OR SWEATING
- IMMEDIATELY AFTER TOWEL DRYING
- AT LEAST EVERY 2 HOURS

• Sun Protection Measures. Spending time in the sun increases your risk of skin cancer and early skin aging. To decrease this risk, regularly use a sunscreen with a broad spectrum SPF of 15 or higher and other sun protection measures including:
o limit time in the sun, especially from 10 a.m.-2 p.m.
o wear long-sleeve shirts, pants, hats, and sunglasses
• Children under 6 months: Ask a doctor

Other Information

Sun alert: Limiting sun exposure, wearing protective clothing, and using sunscreens may reduce the risk of skin cancer, and other harmful effects of the sun.

Questions or Comments?

Call Customer Care at (888) 804-4447

Inactive Ingredients

1,2-Hexanediol, Acrylates/C10-30 Alkyl Acrylate Crosspolymer, Alumina, Butylene Glycol, C12-15 Alkyl Benzoate, Caprylic/Capric Triglyceride, Caprylyl Glycol, Cetearyl Alcohol, Cetearyl Glucoside, Disodium EDTA, Dimethicone, Glyceryl Stearate, Methicone, Octyldodecyl Neopentanoate, PEG-100 Stearate, Polyhydroxystearic Acid, Sorbitan Laurate, Styrene/Acrylates Copolymer, Tocopherol, Tocopheryl Acetate, Triethoxycaprylylsilane, VP/Eicosene Copolymer, Water/Aqua/Eau, Xanthan Gum +/- Iron Oxides.